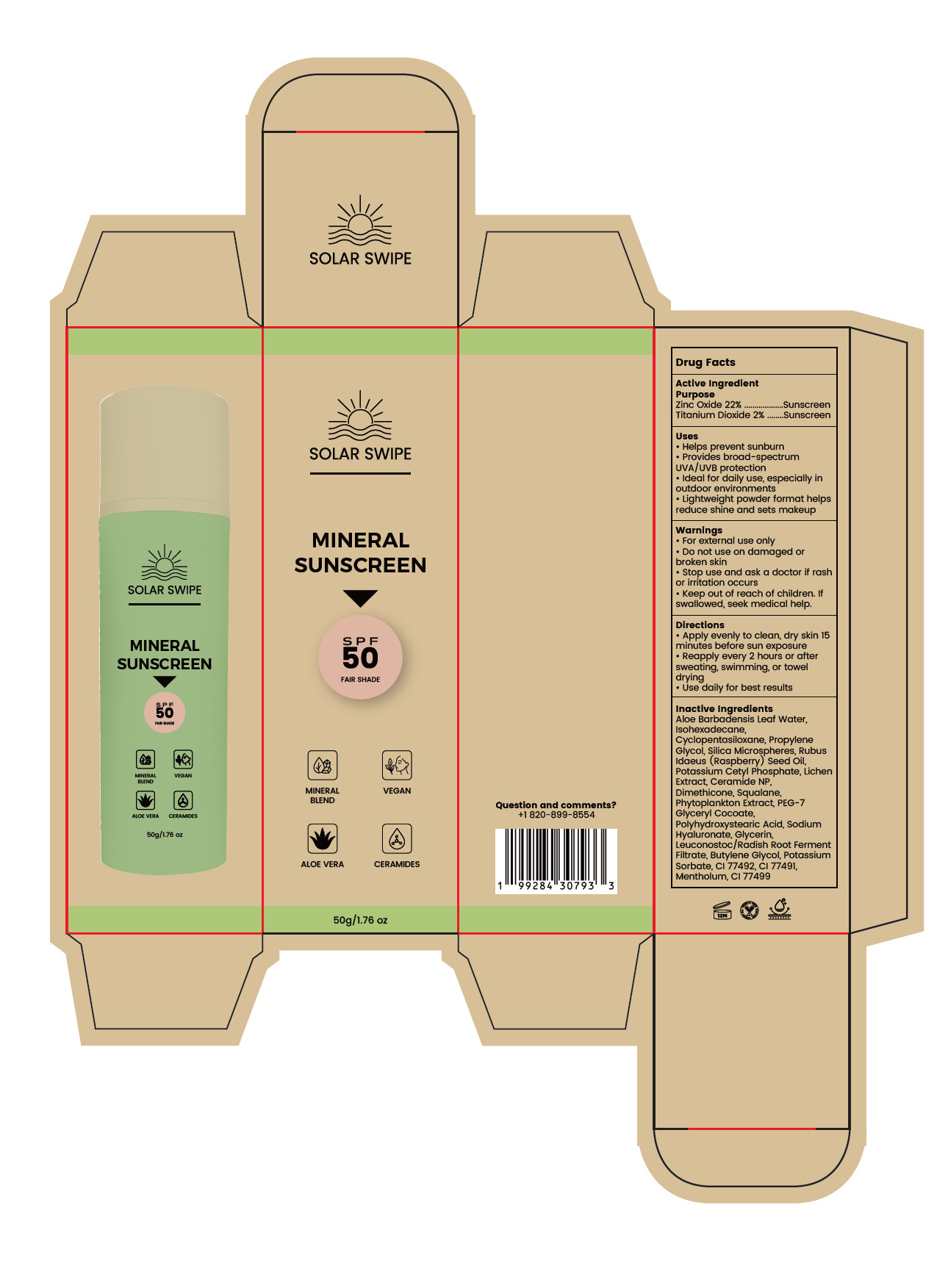 DRUG LABEL: Solar Swipe Mineral Sunscreen SPF50
NDC: 83447-015 | Form: CREAM
Manufacturer: Guangzhou Fantesy Biotechnology Co.,Ltd
Category: otc | Type: HUMAN OTC DRUG LABEL
Date: 20260107

ACTIVE INGREDIENTS: ZINC OXIDE 22 g/100 g; TITANIUM DIOXIDE 2 g/100 g
INACTIVE INGREDIENTS: CYCLOPENTASILOXANE; PROPYLENE GLYCOL; SILICA; RUBUS IDAEUS (RASPBERRY) SEED OIL; POTASSIUM CETYL PHOSPHATE; CERAMIDE NP; DIMETHICONE; SQUALANE; PEG-7 GLYCERYL COCOATE; POLYHYDROXYSTEARIC ACID STEARATE; SODIUM HYALURONATE; GLYCERIN; LEUCONOSTOC/RADISH ROOT FERMENT FILTRATE; BUTYLENE GLYCOL; POTASSIUM SORBATE; CI 77492; CI 77491; MENTHOL; CI 77499; ISOHEXADECANE; WATER

83447-015

Active ingredients

Zinc Oxide 22%
Titanium Dioxide 2%

Purpose

Sunscreen

Uses

1. Helps prevent sunburn
2. Provides broad-spectrum
UVA/UVB protection
1. ldeal for daily use, especially in outdoor environments
2. Lightweight powder format helps reduce shine and sets makeup

Warnings

For external use only

Do not use on damaged or broken skin

When using this product, keep out of eyes. Rinse with water to remove.

Stop use

Stop use and ask a doctor if rash or irritation occurs.

Keep out of reach of children. lf swallowed, seek medical help.

Directions

·Apply evenly to clean, dry skin 15 minutes before sun exposure
·Reapply every 2 hours or after sweating, swimming, or towel drying
·Use daily for best results

Other information

Room temperature preservation

Inactive ingredients

Aloe Barbadensis Leaf Water, Isohexadecane, Cyclopentasiloxane, Propylene Glycol, Silica Microspheres, Rubus
Idaeus (Raspberry) Seed Oil, Potassium Cetyl Phosphate, Lichen Extract, Ceramide NP, Dimethicone, Squalane,
Phytoplankton Extract, PEG-7 Glyceryl Cocoate, Polyhydroxystearic Acid, Sodium Hyaluronate, Glycerin,
Leuconostoc/Radish Root Ferment Filtrate, Butylene Glycol, Potassium Sorbate, CI 77492, CI 77491,
Mentholum, CI 77499